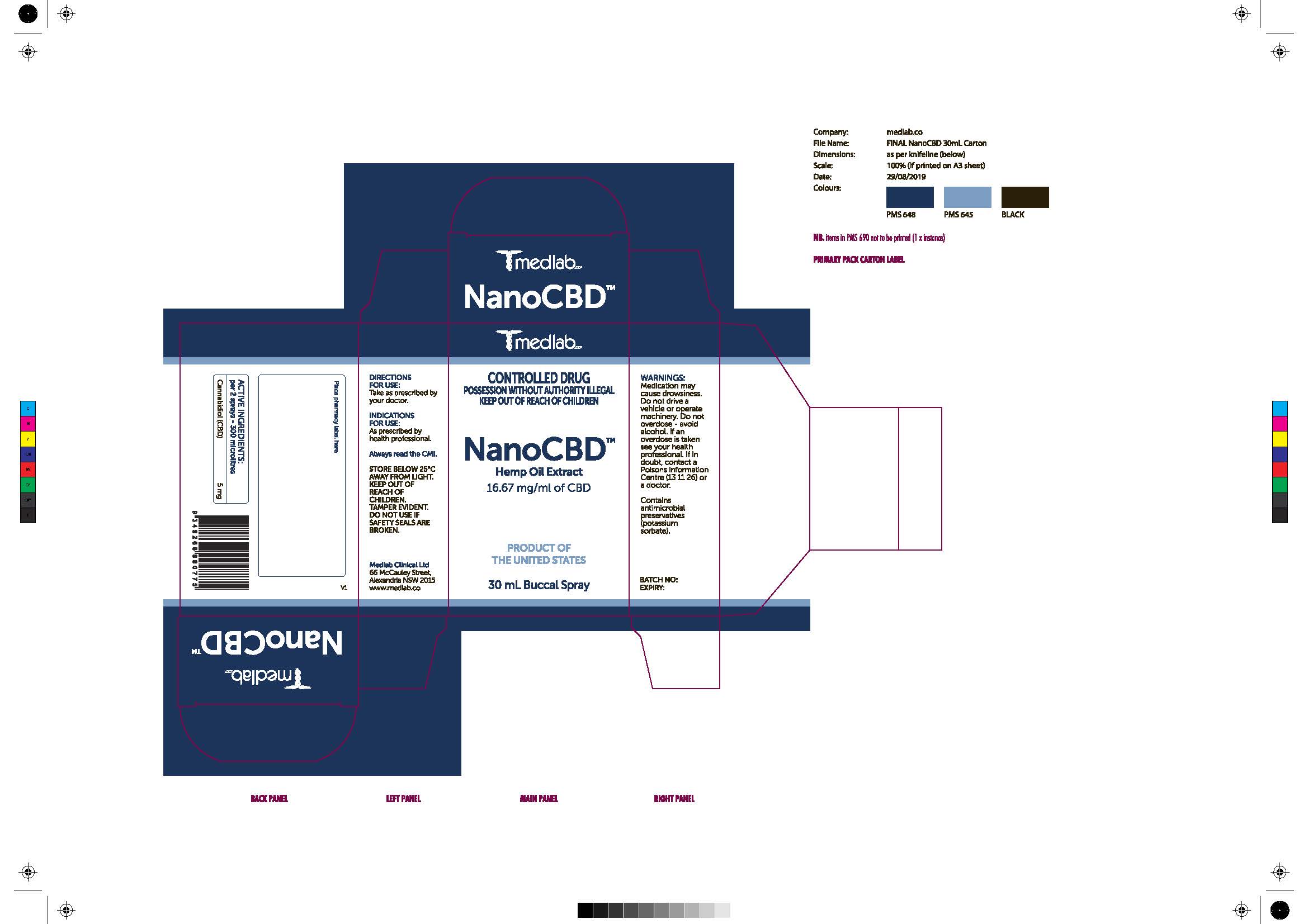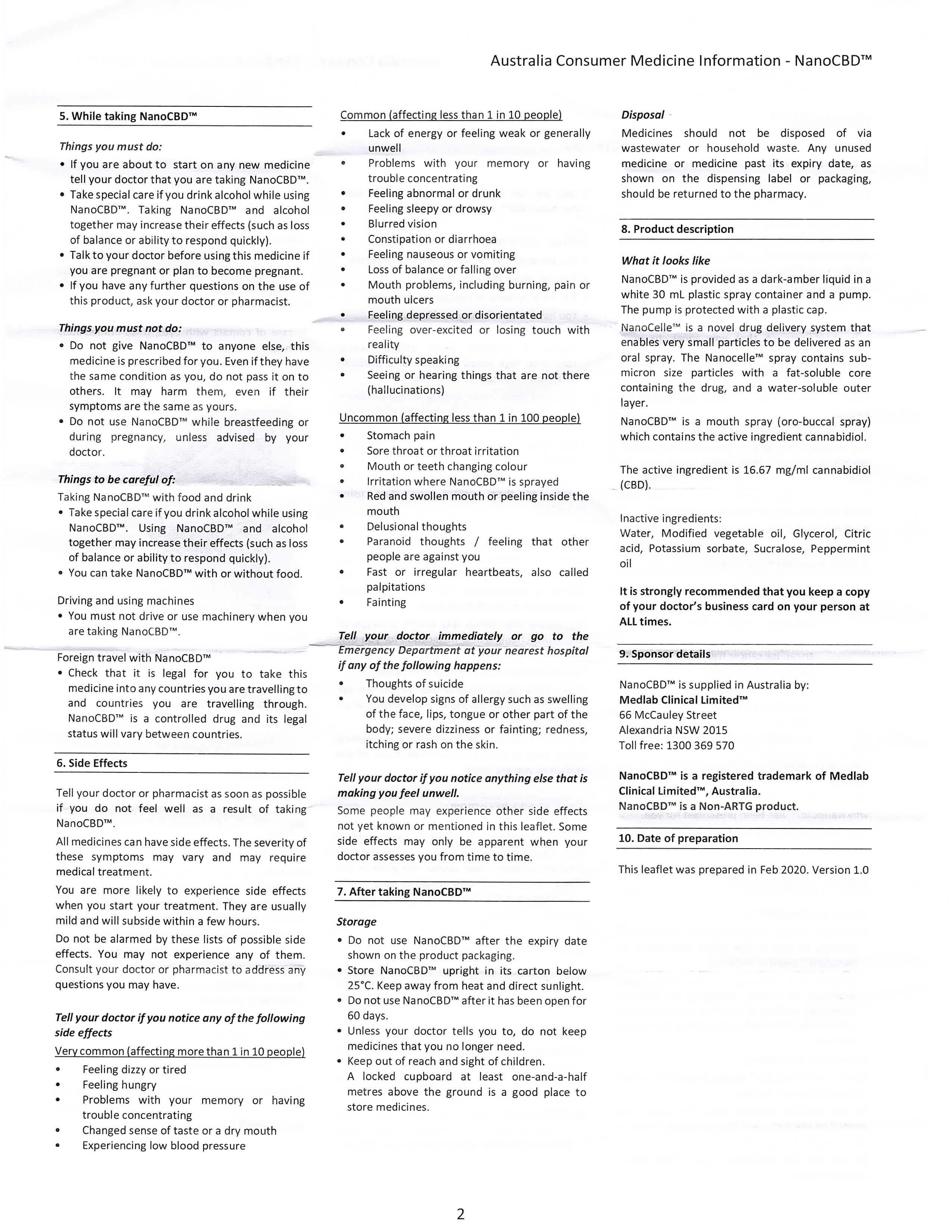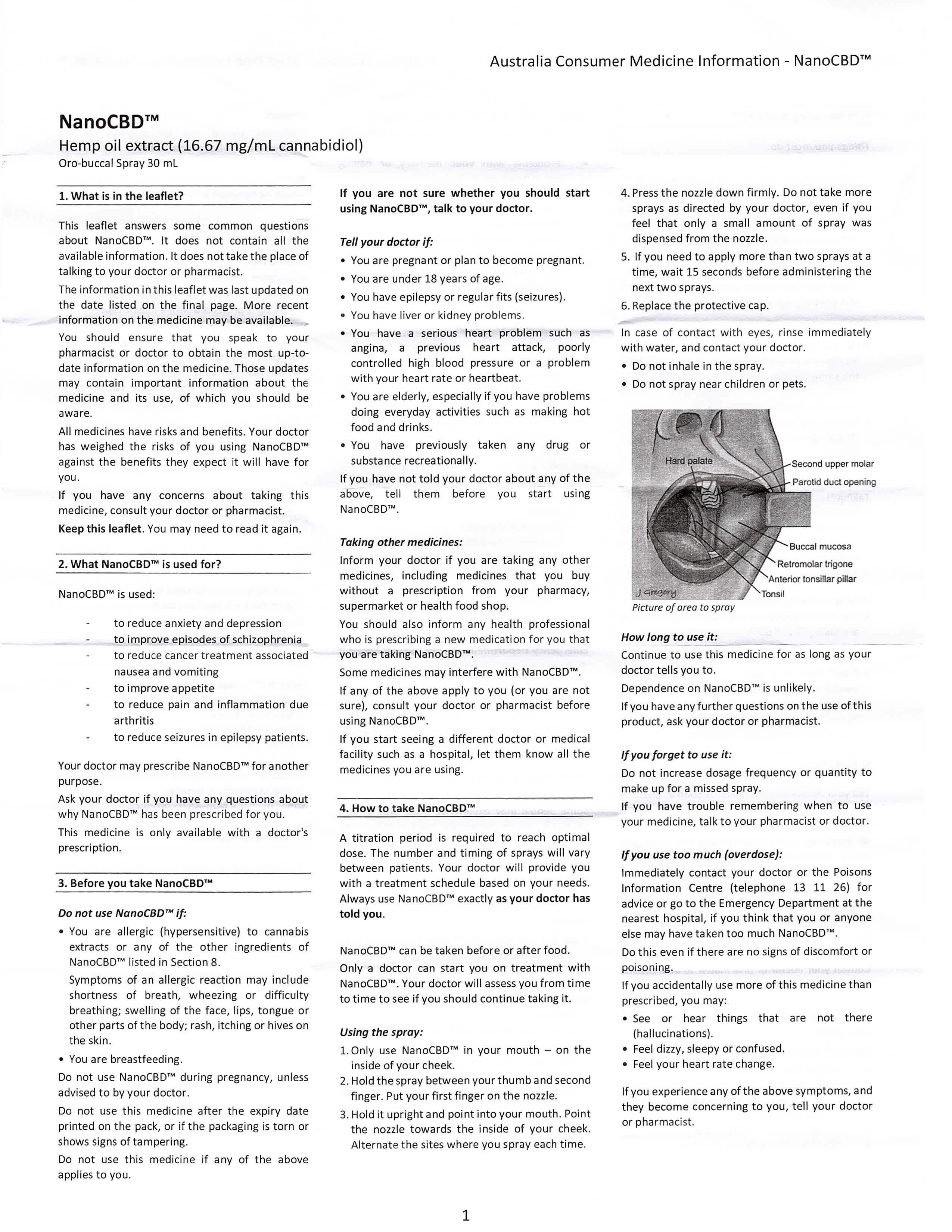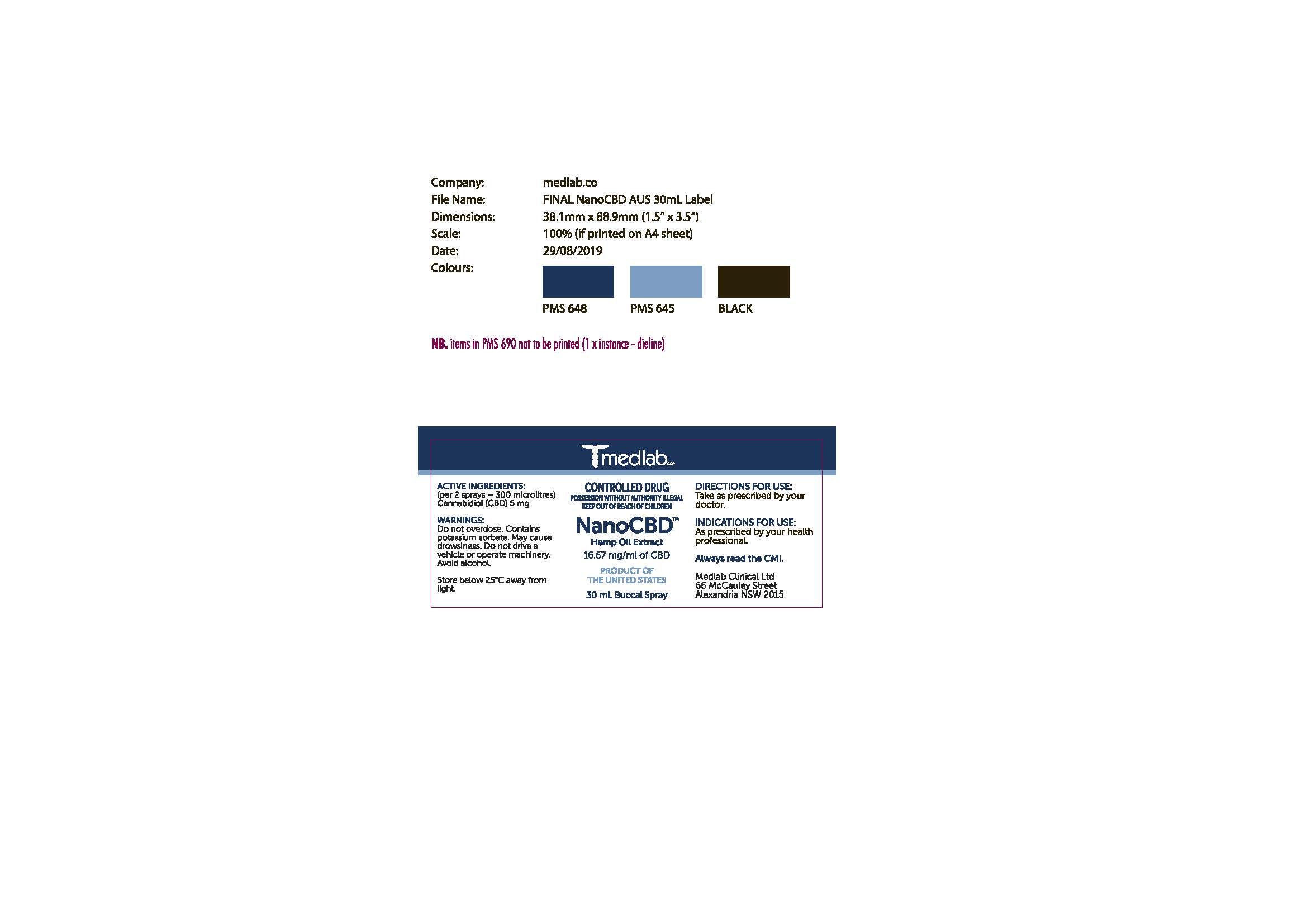 DRUG LABEL: NanoCDB
NDC: 70658-122 | Form: SOLUTION/ DROPS
Manufacturer: Creative Essences Inc
Category: otc | Type: HUMAN OTC DRUG LABEL
Date: 20200421

ACTIVE INGREDIENTS: CANNABIDIOL 1.938 g/100 mL
INACTIVE INGREDIENTS: WATER 77.27 g/100 mL; ANHYDROUS CITRIC ACID 0.096 g/100 mL; GLYCERIN 4.41 g/100 mL; POTASSIUM SORBATE 0.1 g/100 mL; REBAUDIOSIDE A; PEPPERMINT OIL 0.31 g/100 mL; POLYOXYL 40 CASTOR OIL 15.65 g/100 mL

NanoCBD

Warning Section (Carton AU)

Medication may cause drowsiness. Do not drive a vehicle or operate machinery. Do not overdose - avoid alcohol. If an overdoes is taken see your health professional. If in doubt, contact a Poisons Information Centre (13 11 26) or a doctor.

Carton Food Safety Warning

Contains animicrobial preservatives (potassium sorbate).

Indication for Use:

As prescribed by health professionals.

Other Safety Information on Cartons (AU)

Store below 25C away from light. Keep out of reach of children. Tamper Evident. Do not use if safety seals are broken.

Inactive Ingredients on Leaflet (Page 2)

Water, modified vegetable oil, glycerol, citric acid, potassium sorbate, sucralose, peppermint oil

Section 8 of Leaflet

What is looks like

NanoCBD is provided as a dark-amber liquid in a while 30 mL plastic spray container and a pump. The pump is protected with a plastic cup. NanoCelle is a novel drug delivery system that enables very small particles to be delivered as an oral spray. The Nanocelle spray contains submicron size particles with a fat-soluble core containing the drug, and a water-soluble outer layer.

NanoCBD is a mouth spray (oro-buccal spray) wihch contains the active ingredient cannacidiol.

Dosage and Administration on Product Label

Active Ingredient (per 2 sprays - 300 microlitres) Cannabidiol (CBD) 5 mg

Directions for use: Take as prescribed by your doctor.

PDP

See Final NanoCBD AUS 30mL Label Image.